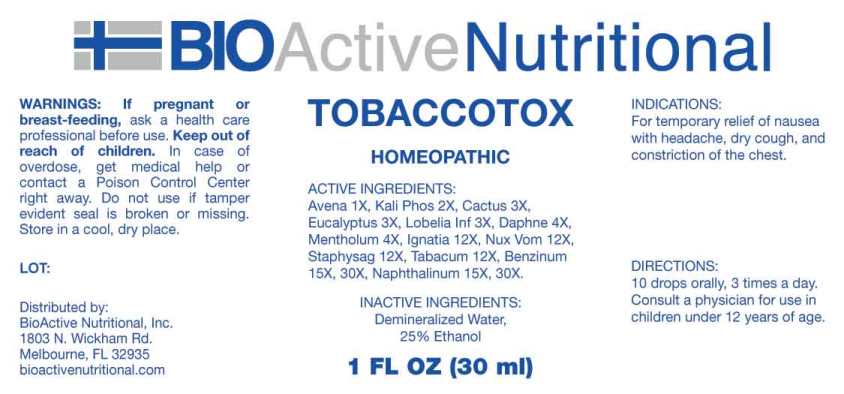 DRUG LABEL: Tobaccotox
NDC: 43857-0578 | Form: LIQUID
Manufacturer: BioActive Nutritional, Inc.
Category: homeopathic | Type: HUMAN OTC DRUG LABEL
Date: 20231013

ACTIVE INGREDIENTS: AVENA SATIVA FLOWERING TOP 1 [hp_X]/1 mL; DIBASIC POTASSIUM PHOSPHATE 2 [hp_X]/1 mL; SELENICEREUS GRANDIFLORUS STEM 3 [hp_X]/1 mL; EUCALYPTUS GLOBULUS LEAF 3 [hp_X]/1 mL; LOBELIA INFLATA WHOLE 3 [hp_X]/1 mL; DAPHNE ODORA BARK 4 [hp_X]/1 mL; MENTHOL, UNSPECIFIED FORM 4 [hp_X]/1 mL; STRYCHNOS IGNATII SEED 12 [hp_X]/1 mL; STRYCHNOS NUX-VOMICA SEED 12 [hp_X]/1 mL; DELPHINIUM STAPHISAGRIA SEED 12 [hp_X]/1 mL; TOBACCO LEAF 12 [hp_X]/1 mL; BENZENE 15 [hp_X]/1 mL; NAPHTHALENE 15 [hp_X]/1 mL
INACTIVE INGREDIENTS: WATER; ALCOHOL

DRUG FACTS:

ACTIVE INGREDIENTS:

Avena Sativa 1X, Kali Phosphoricum 2X, Cactus Grandiflorus 3X, Eucalyptus Globulus 3X, Lobelia Inflata 3X, Daphne Indica 4X, Mentholum 4X, Ignatia Amara 12X, Nux Vomica 12X, Staphysagria 12X, Tabacum 12X, Benzinum 15X, 30X, Naphthalinum 15X, 30X

INDICATIONS:

For temporary relief of nausea with headache, dry cough, and constriction of the chest.

WARNINGS:

If pregnant or breast-feeding, ask a health care professional before use.

Keep out of reach of children. In case of overdose, get medical help or contact a Poison Control Center right away.

Do not use if tamper evident seal is broken or missing.

Store in cool, dry place.

KEEP OUT OF REACH OF CHILDREN:

In case of overdose, get medical help or contact a Poison Control Center right away.

DIRECTIONS:

10 drops orally, 3 times a day. Consult a physician for use in children under 12 years of age.

INDICATIONS:

For temporary relief of nausea with headache, dry cough, and constriction of the chest.

INACTIVE INGREDIENTS:

Demineralized water, 25% Ethanol

QUESTIONS:

Distributed by:
BioActive Nutritional, Inc.
1803 N. Wickham Rd.
Melbourne, FL 32935
bioactivenutritional.com

PACKAGE LABEL DISPLAY:

BIOActive Nutritional

TOBACCOTOX

HOMEOPATHIC

1 FL OZ (30 ml)